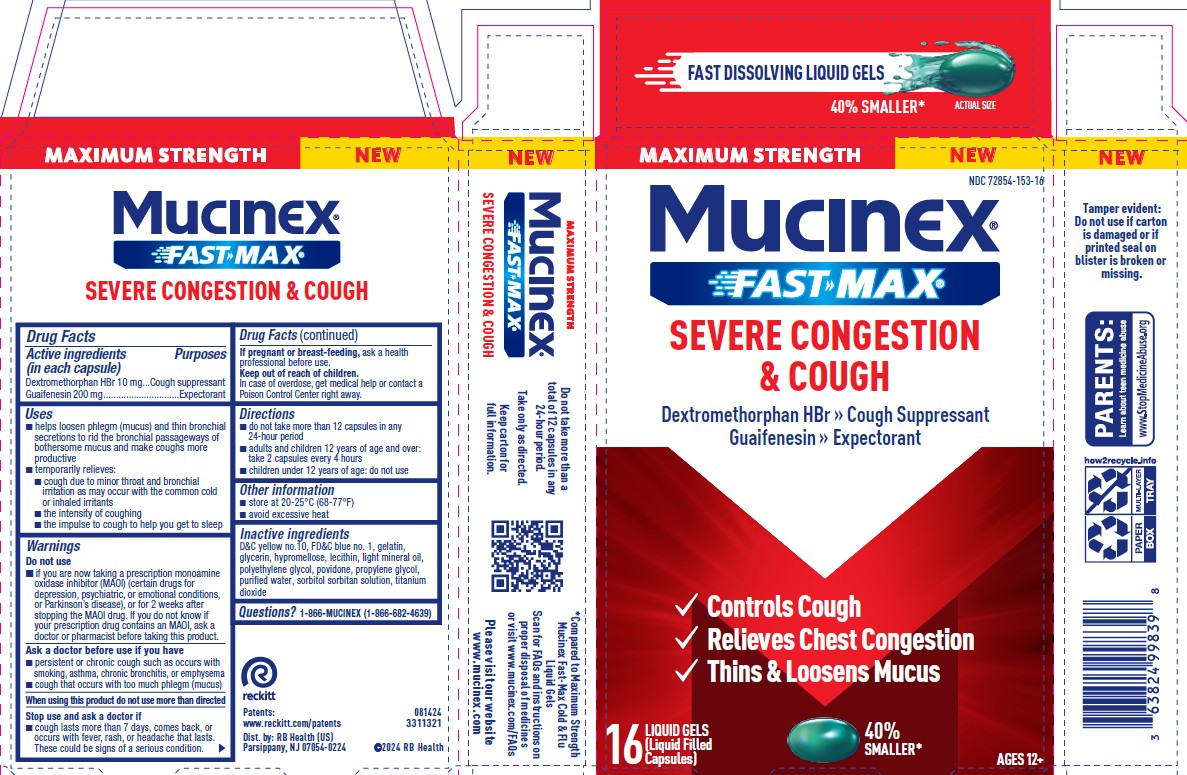 DRUG LABEL: Mucinex Fast-Max Severe Congestion and Cough
NDC: 72854-153 | Form: CAPSULE, LIQUID FILLED
Manufacturer: RB Health (US) LLC
Category: otc | Type: HUMAN OTC DRUG LABEL
Date: 20251105

ACTIVE INGREDIENTS: DEXTROMETHORPHAN HYDROBROMIDE 10 mg/1 1; GUAIFENESIN 200 mg/1 1
INACTIVE INGREDIENTS: POVIDONE; WATER; GLYCERIN; HYPROMELLOSES; POLYETHYLENE GLYCOL, UNSPECIFIED; FD&C BLUE NO. 1; D&C YELLOW NO. 10; LECITHIN, SOYBEAN; LIGHT MINERAL OIL; PROPYLENE GLYCOL; GELATIN; TITANIUM DIOXIDE; SORBITOL SOLUTION

Mucinex Fast-Max Severe Congestion & Cough

Active ingredients (in each liquid gel) | Purposes
Dextromethorphan HBr 10 mg | Cough suppressant
Guaifenesin 200 mg | Expectorant

Keep out of reach of children.
In case of overdose, get medical help or contact a
Poison Control Center right away.

PURPOSE

Dextromethorphan HBr 10 mg....Cough suppressant
Guaifenesin 200mg...............................Expectorant

Uses

■ helps loosen phlegm (mucus) and thin bronchial
secretions to rid the bronchial passageways of
bothersome mucus and make coughs more
productive

Temporarily relieves:
■ cough due to minor throat and bronchial
irritation as may occur with the common cold or
inhaled irritants
■ the intensity of coughing
■ the impulse to cough to help you get to sleep

Do not use:
■ if you are now taking a prescription monoamine
oxidase inhibitor (MAOI) (certain drugs for
depression, psychiatric, or emotional conditions,
or Parkinson’s disease), or for 2 weeks after
stopping the MAOI drug. If you do not know if your
prescription drug contains an MAOI, ask a doctor
or pharmacist before taking this product.

Ask a doctor before use if you have
■ persistent or chronic cough such as occurs with
smoking, asthma, chronic bronchitis, or emphysema
■ cough that occurs with too much phlegm (mucus)

When using this product do not use more than directed

Stop use and ask a doctor if
■ cough lasts more than 7 days, comes back, or
occurs with fever, rash, or headache that lasts.
These could be signs of a serious condition.

If pregnant or breast-feeding, ask a health
professional before use.

Keep out of reach of children.
In case of overdose, get medical help or contact a
Poison Control Center right away.

Directions

■ do not take more than 12 capsules in any
24-hour period
■ adults and children 12 years of age and over:
take 2 capsules every 4 hours
■ children under 12 years of age: do not use

OTHER SAFETY INFORMATION

■ store at 20-25°C (68-77°F)
■ avoid excessive heat

Inactive ingredients
D&C yellow no.10, FD&C blue no. 1, gelatin,
glycerin, hypromellose, lecithin, light mineral oil,
polyethylene glycol, povidone, propylene glycol,
purified water, sorbitol sorbitan solution, titanium
dioxide

Questions? 1-866-MUCINEX (1-866-682-4639)

PACKAGE LABEL

Fast Dissolving Liquid Gels!

NDC 72854-153

MAXIMUM STRENGTH

MUCINEX®
FAST-MAX ®